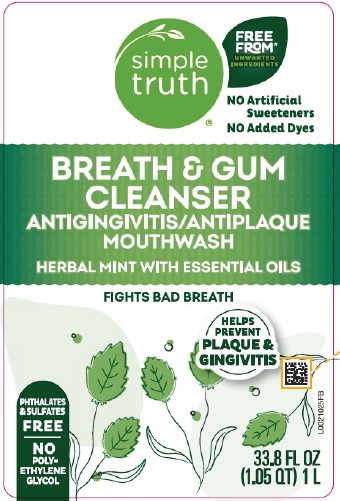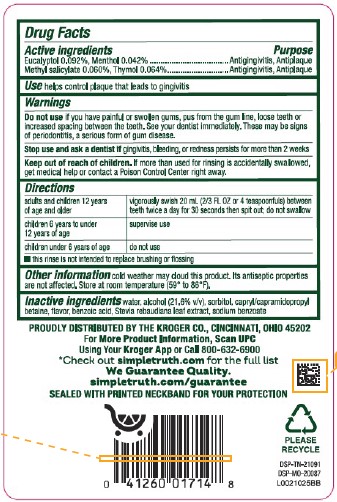 DRUG LABEL: Mouth Rinse
NDC: 59450-901 | Form: MOUTHWASH
Manufacturer: The Kroger Co.
Category: otc | Type: HUMAN OTC DRUG LABEL
Date: 20260227

ACTIVE INGREDIENTS: EUCALYPTOL 0.92 mg/1 mL; MENTHOL 0.42 mg/1 mL; METHYL SALICYLATE 0.6 mg/1 mL; THYMOL 0.64 mg/1 mL
INACTIVE INGREDIENTS: WATER; ALCOHOL; SORBITOL; CAPRYL/CAPRAMIDOPROPYL BETAINE; BENZOIC ACID; STEVIA REBAUDIUNA LEAF; SODIUM BENZOATE

Kroger Simple Truth D01.000/D01AA rev 1
Herbal Mint Antiseptic Mouthwash

Active ingredients

Eucalyptol 0.092%

Menthol 0.042%

Methyl salicylate 0.060%

Thymol 0.064%

Purpose

Antigingivitis, Antiplaque

Use

helps control plaque that leads to gingivitis

Warnings

for this product

Do not use

if you have painful or swollen gums, pus from the gum line, loose teeth or increased spacing between the teeth. See your dentist immediately. These may be signs of periodontitis, a serious form of gum disease.

Stop use and ask a dentist if

gingivitis, bleeding, or redness persists for more than 2 weeks

Keep out of reach of children.

If more than used for rinsing is accidentally swallowed, get medical help or contact a Poison Control Center right away.

Directions

adults and children 12 years of age and older - vigorously swish 20 mL (2/3 FL OZ or 4 teaspoonfuls) between teeth twice a day for 30 seconds then spit out; do not swallow

children 6 years to under 12 years of age - supervise use

children under 6 years of age - do not use

- this rinse is not intended to replace brushing or flossing

Other information

cold weather may cloud this product. Its antiseptic properties are not affected. Store at room temperature (59° to 86°F).

Inactive ingredients

water, alcohol (21.6% v/v), sorbitol, capryl/capramidopropyl betaine, flavor, benzoic acid, Stevia rebaudiana leaf extract, sodium benzoate

ADVERSE REACTION

PROUDLY DISTRIBUTED BY THE KROGER CO., CINCINNATI, OHIO 45202

For More Product Information, Scan UPC Using Your Kroger App or Call 800-632-6900

*Check out simpletruth.com for full list

We Guarantee Quality.

simpletruth.com/guarantee

SEALED WITH PRINTED NECKBAND FOR YOUR PROTECTION

PLEASE RECYCLE

DSP-TN-21091

DSP-MO-20087

Principal Panel Display

simple truth®

FREE FROM*

UNWANTED INGREDIENTS

NO Artificial Sweetners

NO Added Dyes

Breath & Gum Cleanser

ANTIGINGIVITIS/ANTIPLAQUE MOUTHWASH

HERBAL MINT WITH ESSENTIAL OILS

Fights Bad Breath

Helps Prevent Plaque & Gingivitis

PHTHALATES & SULFATES FREE

NO POLY-ETHYLENE GLYCOL

33.8 FL OZ (1.05 QT) 1 L